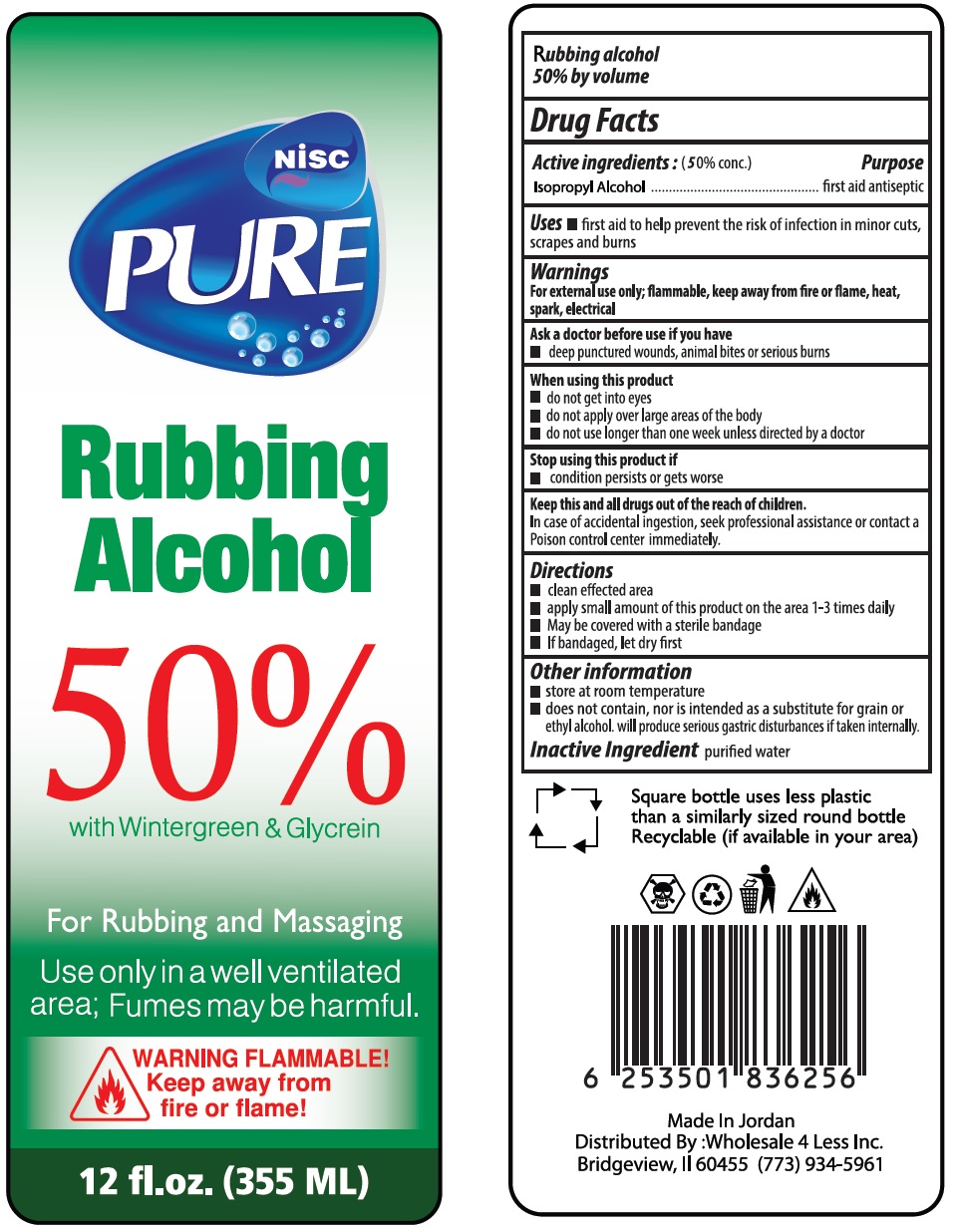 DRUG LABEL: NISC Pure 50% with Wintergreen and Glycerin
NDC: 75771-120 | Form: LIQUID
Manufacturer: NOWREZ & ISMAIL SHUKRI COMPANY
Category: otc | Type: HUMAN OTC DRUG LABEL
Date: 20210309

ACTIVE INGREDIENTS: ISOPROPYL ALCOHOL 50 mL/100 mL
INACTIVE INGREDIENTS: WATER; METHYL SALICYLATE; GLYCERIN

Nisc PURE 50% Rubbing Alcohol with Wintergreen & Glycerin

Active ingredients : (50% conc.)

Isopropyl Alcohol

Purpose

first aid antiseptic

Uses

• first aid to help prevent the risk of infection in minor cuts, scrapes and burns

Warnings

For external use only; flammable, keep away from fire or flame, heat, spark, electrical

Ask a doctor before use if you have

• deep punctured wounds, animal bites or serious burns

When using this product

• do not get into eyes

• do not apply over large areas of the body

• do not use longer than one week unless directed by a doctor

Stop using this product if

• condition persists or gets worse

KEEP OUT OF REACH OF CHILDREN

Keep this and all drugs out of the reach of children.

In case of accidental ingestion, seek professional assistance or contact a Poison control center immediately.

Directions

• clean affected area

• apply small amount of this product on the area 1-3 times daily

• May be covered with a sterile bandage

• If bandaged, let dry first

Other information

• store at room temperature

• does not contain, nor is intended as a substitute for grain or ethyl alcohol. will produce serious gastric disturbances if taken internally.

Inactive Ingredient

purified water, wintergreen, glycerin

For Rubbing and Massaging

Use only in a well ventilated area; Fumes may be harmful.

WARNING FLAMMABLE!

Keep away from fire or flame!

Rubbing alcohol 50% by volume

Square bottle uses less plastic than a similarly sized round bottle

Recyclable (if available in your area)

Made In Jordan

Distributed By :Wholesale 4 Less Inc.

Bridgeview, Il 60455 (773) 934-5961